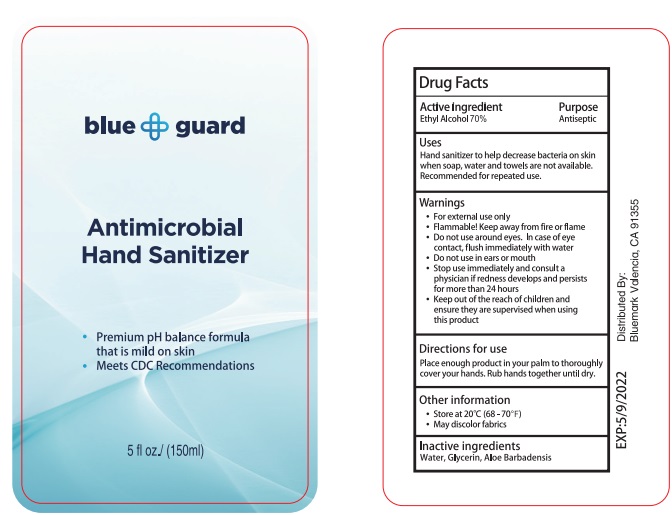 DRUG LABEL: blue guard Hand Sanitizer
NDC: 75780-004 | Form: GEL
Manufacturer: NINGBO MEINEKE Biotech Technology Co., Ltd.
Category: otc | Type: HUMAN OTC DRUG LABEL
Date: 20200522

ACTIVE INGREDIENTS: alcohol 70 mL/100 mL
INACTIVE INGREDIENTS: WATER; PROPYLENE GLYCOL; ALOE VERA LEAF; CARBOMER 934; GLYCERIN

Drug facts

Active ingredient Purpose

Ethyl Alcohol 70% ... Antimicrobial

PURPOSE

Hand sanitizer to help decrease bacteria on the skin, when soap, water and towels are not available. Recommended for repeated use.

KEEP OUT OF REACH OF CHILDREN

Ensure they are supervised when using this product.

INDICATIONS AND USAGE

keep out of eyes

when water, soap and towel are not available

WARNINGS

- For external use only.
- Flammable. Keep away from fire or flame.
- Do not use around eyes. In case of eyes contact, flush immediately with water
- Do not use in ears or mouth
- Stop use immediately and consult a physiccian if redness develops and persists for more than 72 hours.

Other information:

Store at 20℃ (68-70℉）

May discolor fabrics

DOSAGE AND ADMINISTRATION

place enough product in your palm to thoroughly cover your hands. Rub hands together until dry

INACTIVE INGREDIENT

Water, Aloe Barbadenis, Glycerin